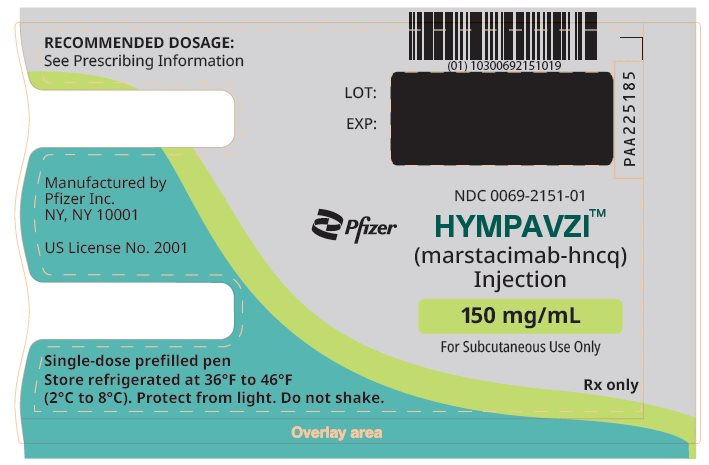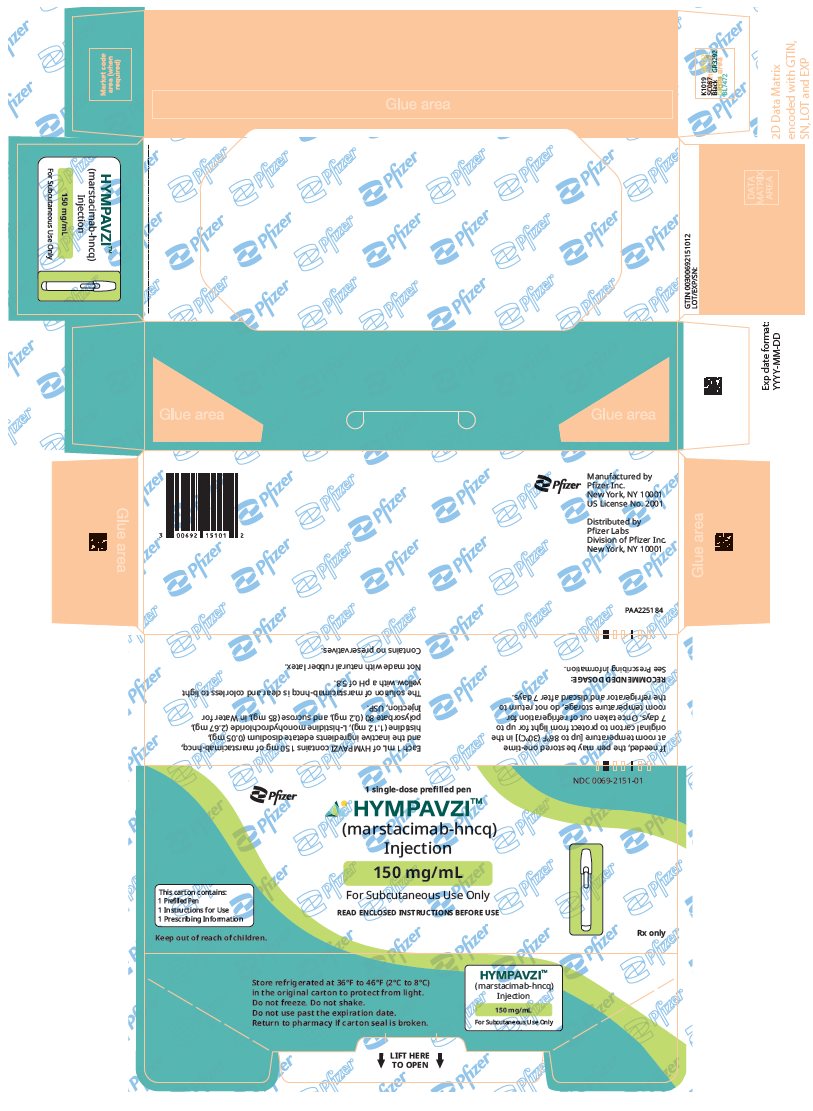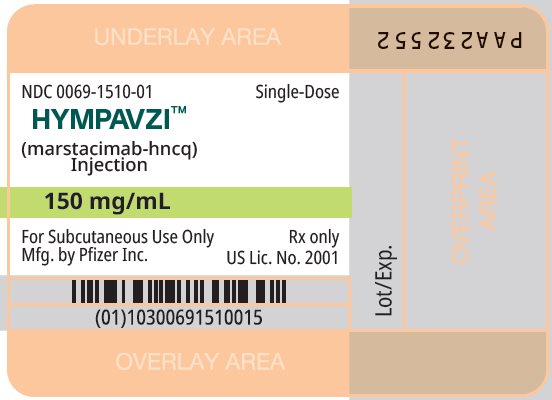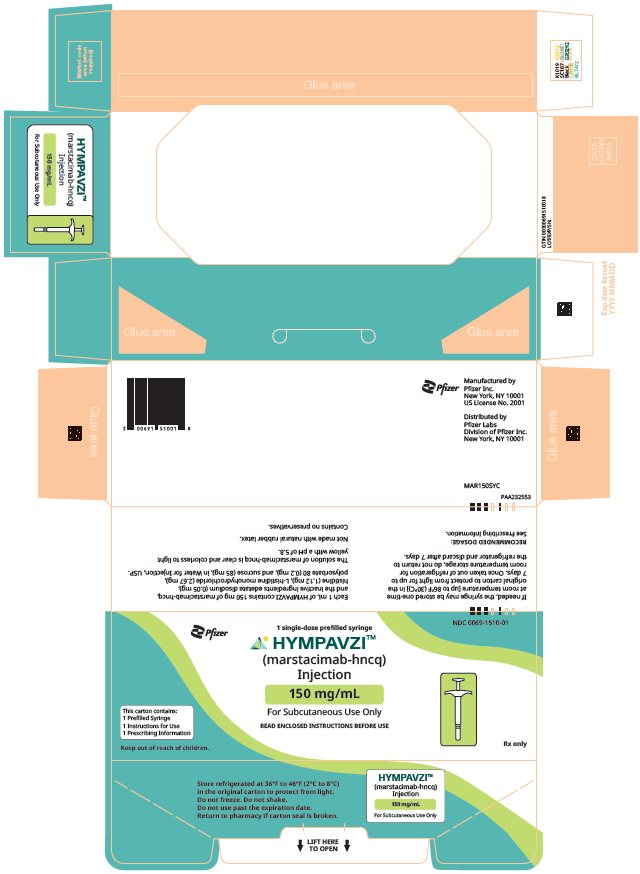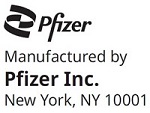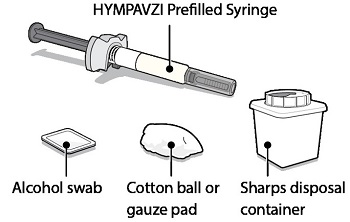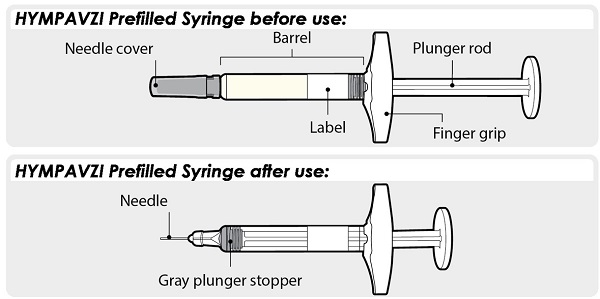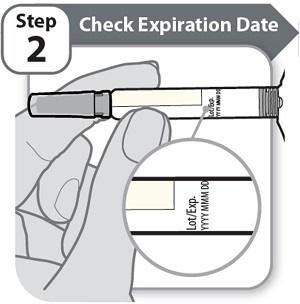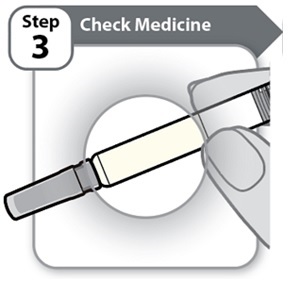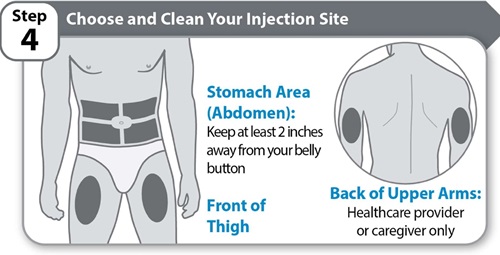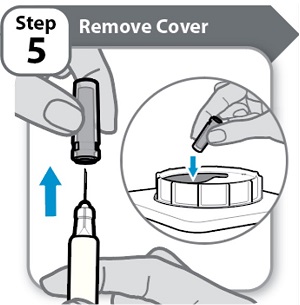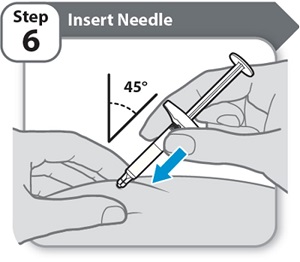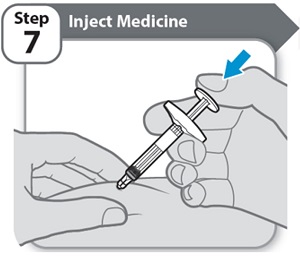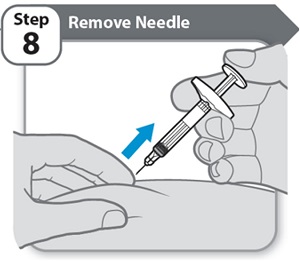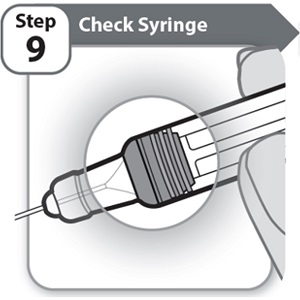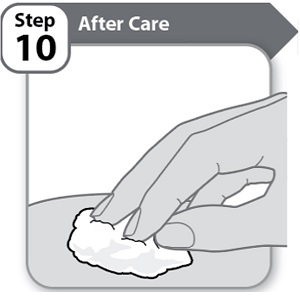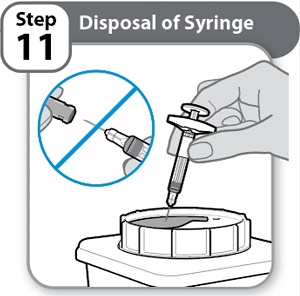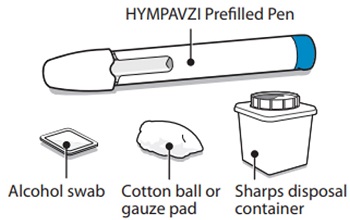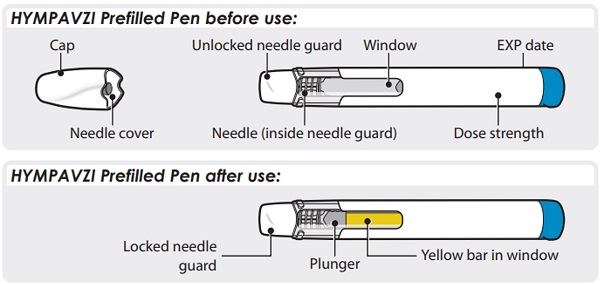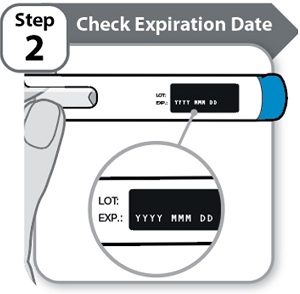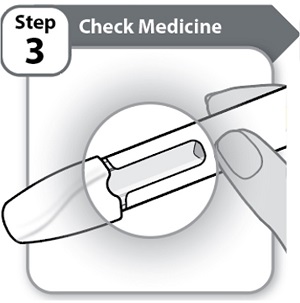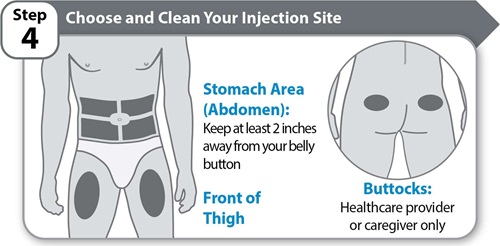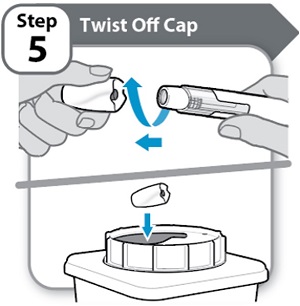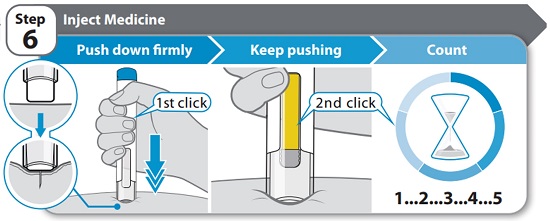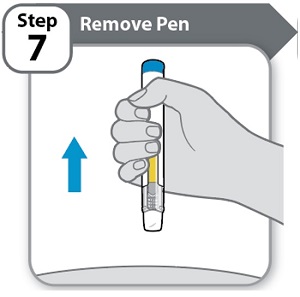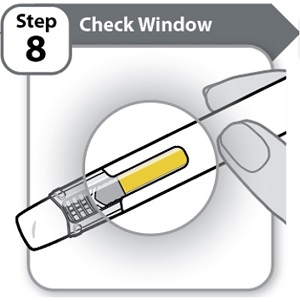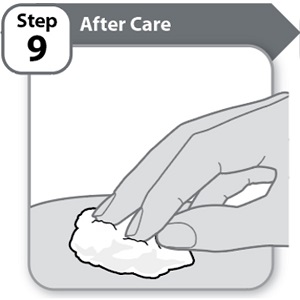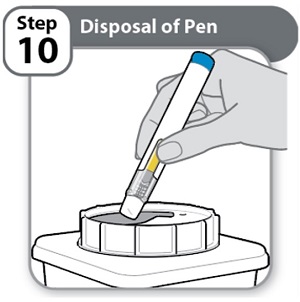 DRUG LABEL: HYMPAVZI
NDC: 0069-2151 | Form: INJECTION, SOLUTION
Manufacturer: Pfizer Laboratories Div Pfizer Inc
Category: prescription | Type: HUMAN PRESCRIPTION DRUG LABEL
Date: 20251218

ACTIVE INGREDIENTS: MARSTACIMAB 150 mg/1 mL
INACTIVE INGREDIENTS: HISTIDINE 1.12 mg/1 mL; HISTIDINE MONOHYDROCHLORIDE MONOHYDRATE 2.67 mg/1 mL; SUCROSE 85 mg/1 mL; EDETATE DISODIUM 0.05 mg/1 mL; POLYSORBATE 80 0.2 mg/1 mL; WATER

HIGHLIGHTS OF PRESCRIBING INFORMATION

These highlights do not include all the information needed to use HYMPAVZI safely and effectively. See full prescribing information for HYMPAVZI.
HYMPAVZI (marstacimab-hncq) injection, for subcutaneous use
Initial U.S. Approval: 2024

1 INDICATIONS AND USAGE

HYMPAVZI is a tissue factor pathway inhibitor (TFPI) antagonist indicated for routine prophylaxis to prevent or reduce the frequency of bleeding episodes in adult and pediatric patients 12 years of age and older with:

- hemophilia A (congenital factor VIII deficiency) without factor VIII inhibitors, or
- hemophilia B (congenital factor IX deficiency) without factor IX inhibitors. (1)

2 DOSAGE AND ADMINISTRATION

- See Full Prescribing Information for important dosing and administration instructions. (2.1, 2.2, 2.3, 2.4, 2.5, 2.6)
- The recommended dosage of HYMPAVZI is:
  - Loading dose: 300 mg (two 150 mg injections) by subcutaneous injection
  - Maintenance dose: One week after the loading dose, initiate maintenance dosing of 150 mg every week by subcutaneous injection on the same day each week, at any time of day. (2.1)
- Dose adjustment to 300 mg subcutaneous injection weekly can be considered. (2.1)
- Factor VIII and factor IX products can be administered for the treatment of breakthrough bleeds in patients receiving HYMPAVZI. Do not use additional doses of HYMPAVZI to treat breakthrough bleeds. (2.4)
- Temporarily discontinue HYMPAVZI before major surgery. (2.5)

3 DOSAGE FORMS AND STRENGTHS

- Injection: 150 mg/mL in a single-dose prefilled syringe (3)
- Injection: 150 mg/mL in a single-dose prefilled pen (3)

4 CONTRAINDICATIONS

None. (4)

5 WARNINGS AND PRECAUTIONS

- Thromboembolic Events: Thromboembolic events may occur. Interrupt HYMPAVZI prophylaxis if symptoms occur. (5.1)
- Hypersensitivity: Hypersensitivity reactions may occur. In the event of a severe allergic reaction, discontinue HYMPAVZI. (5.2)
- Embryofetal Toxicity: May cause fetal harm. Advise females of reproductive potential of the potential risk to the fetus and to use effective contraception. (5.3, 8.1, 8.3)

6 ADVERSE REACTIONS

Adverse reactions reported in ≥3% of HYMPAVZI-treated patients were injection site reaction, headache, and pruritus. (6.1)

To report SUSPECTED ADVERSE REACTIONS, contact Pfizer Inc. at 1-800-438-1985 or FDA at 1-800-FDA-1088 or www.fda.gov/medwatch.

FULL PRESCRIBING INFORMATION

1 INDICATIONS AND USAGE

HYMPAVZI is indicated for routine prophylaxis to prevent or reduce the frequency of bleeding episodes in adult and pediatric patients 12 years of age and older with:

- hemophilia A (congenital factor VIII deficiency) without factor VIII inhibitors, or
- hemophilia B (congenital factor IX deficiency) without factor IX inhibitors.

2 DOSAGE AND ADMINISTRATION

2.1 Recommended Dosage

For subcutaneous use only.
The recommended dosage of HYMPAVZI for adult and pediatric patients 12 years of age and older is as follows:

Loading Dose
300 mg (two 150 mg subcutaneous injections)
If more than one injection is required to deliver a complete dose, administer each injection at a different injection site.

Maintenance Dose
One week after the loading dose, initiate maintenance dosing of 150 mg every week by subcutaneous injection on the same day each week, at any time of day.

Dose Adjustment During Treatment
Consider a dose adjustment to 300 mg subcutaneous injection weekly in patients weighing greater than or equal to 50 kg when control of bleeding events is judged to be inadequate by the healthcare provider. Safety and efficacy of HYMPAVZI at doses above 300 mg weekly have not been established.

If more than one injection is required to deliver a complete dose, administer each injection at a different injection site.

Missed Doses
For patients on a maintenance dose of 150 mg:
If a dose is missed, administer as soon as possible before the day of the next scheduled dose, and then resume usual 150 mg subcutaneous weekly dosing schedule (same schedule as prior to the missed dose or new schedule based on date of administration of missed dose).

If more than 13 days have passed since the last dose was administered, administer a loading dose of 300 mg by subcutaneous injection followed by a resumption of 150 mg by subcutaneous injection once weekly thereafter.

For patients on a maintenance dose of 300 mg:
If one or more doses are missed, administer a dose as soon as possible, and then resume 300 mg subcutaneous weekly dosing schedule (same schedule as prior to the missed dose or new schedule based on date of administration of missed dose).

2.2 Preparation and Administration

- HYMPAVZI is intended for use under the guidance of a healthcare provider. After proper training in subcutaneous injection technique, a patient may self-inject or the patient’s caregiver may administer HYMPAVZI, if a healthcare provider determines that it is appropriate.
- Refer to the Instructions for Use for complete preparation and administration instructions.
- Prior to subcutaneous administration, HYMPAVZI may be removed from the refrigerator and allowed to warm at room temperature [up to 86°F (30°C)] in the carton for 15 to 30 minutes protected from direct sunlight. Do not warm by using a heat source such as hot water or a microwave. After removal of HYMPAVZI from the refrigerator, use within 7 days or discard [see How Supplied/Storage and Handling (16)].
- Administer HYMPAVZI by subcutaneous injection, once weekly, at any time of the day in the abdomen or front of thigh. Other injection sites are acceptable if required. Administration of HYMPAVZI in the back of upper arm (prefilled syringe only) or buttocks (prefilled pen only) should be performed by a caregiver or healthcare professional only. HYMPAVZI should not be administered into bony areas or areas where the skin is bruised, red, tender or hard, or areas where there are scars or stretch marks. HYMPAVZI should not be injected into a vein. Rotate the injection site with each new injection.
- During treatment with HYMPAVZI, other medicinal products for subcutaneous administration should, preferably, be injected at different anatomical sites.
- Parenteral drug products should be inspected visually for particulate matter and discoloration prior to administration, whenever solution and container permit. HYMPAVZI is a clear and colorless to light yellow solution. Do not use if the solution is cloudy, dark yellow, or contains flakes or particles.

2.3 Changing to HYMPAVZI

Changing from prophylactic factor replacement therapy to HYMPAVZI: Prior to initiation of HYMPAVZI, discontinue treatment with clotting factor concentrates (factor VIII or factor IX concentrates). HYMPAVZI can be initiated at any time after discontinuing clotting factor concentrates.

No data are available in patients changing from non-factor-based hemophilia medicinal products to HYMPAVZI.

2.4 Guidance on Use with Breakthrough Bleed Treatments

Factor VIII and factor IX products can be administered for the treatment of breakthrough bleeds in patients receiving HYMPAVZI. Do not use additional doses of HYMPAVZI to treat breakthrough bleeds. Healthcare providers should discuss with all patients and/or caregivers the dose and schedule of clotting factor concentrates to use, if required, while receiving HYMPAVZI prophylaxis, including using the lowest possible effective dose of clotting factor concentrate [see Warnings and Precautions (5.1)]. Please refer to the Full Prescribing Information for the clotting factor concentrate being used.

2.5 Temporary Interruption for Surgery and Other Interventions

Management in the Perioperative Setting
HYMPAVZI has not been evaluated in the setting of major surgery. Patients have had minor surgical procedures without discontinuing HYMPAVZI prophylaxis in clinical studies.

For major surgery, discontinue HYMPAVZI and initiate management per local standard of care with clotting factor concentrate and measures to manage the risk of venous thrombosis which can be elevated in the perioperative period. Consult the product information for the clotting factor concentrate for dosage guidelines in patients with hemophilia undergoing major surgery. Resumption of HYMPAVZI therapy should consider the overall clinical status of the patient, including the presence of post-surgical thromboembolic risk factors, use of other hemostatic products and other concomitant medications [see Dosage and Administration (2.1)].

Management in Patients with Acute Severe Illness
There is limited experience with the use of HYMPAVZI in patients with acute severe illness. Reasons to consider temporary dose interruption of HYMPAVZI include occurrence of acute severe illness (e.g., serious infection, sepsis, trauma) in which there may be increased activation of coagulation and which the healthcare provider considers could increase the risks associated with HYMPAVZI administration. Treatment of acute severe illness should be managed per local standard of care, and continued treatment with HYMPAVZI in this situation should be weighed against the potential risks involved. Resume HYMPAVZI therapy once patient has clinically recovered [see Dosage and Administration (2.1)].

2.6 Pregnancy Testing

Verify that females of reproductive potential are not pregnant prior to initiating HYMPAVZI [see Warnings and Precautions (5.3), Use in Specific Populations (8.1, 8.3)].

3 DOSAGE FORMS AND STRENGTHS

HYMPAVZI (marstacimab‑hncq) is a clear and colorless to light yellow solution available as:

Prefilled Syringe

- Injection: 150 mg/mL in a single-dose prefilled syringe

Prefilled Pen

- Injection: 150 mg/mL in a single-dose prefilled pen

4 CONTRAINDICATIONS

None.

5 WARNINGS AND PRECAUTIONS

5.1 Thromboembolic Events

HYMPAVZI is a tissue factor pathway inhibitor (TFPI) antagonist, and may increase the risk of thromboembolic complications. Venous thrombotic events were reported in clinical studies with HYMPAVZI [see Adverse Reactions (6.1)].

Patients with independent risk factors for thromboembolic events may be at increased risk of thromboembolic events with use of HYMPAVZI.

HYMPAVZI has not been studied in patients with a history of previous thromboembolic events [see Clinical Studies (14.1)]. Consider the benefit and risk of using HYMPAVZI in patients with known risk factors for thromboembolism.

Interrupt HYMPAVZI prophylaxis if diagnostic findings consistent with thromboembolism occur and manage as clinically indicated.

If factor VIII or factor IX products are indicated in a patient receiving HYMPAVZI prophylaxis, the minimum effective dose of factor VIII or factor IX according to the product label is recommended [see Dosage and Administration (2.4)].

5.2 Hypersensitivity

HYMPAVZI may cause hypersensitivity reactions (including, but not limited to urticaria and pruritus). If HYMPAVZI-treated patients develop a severe hypersensitivity reaction, advise patients to discontinue HYMPAVZI and seek immediate emergency treatment.

5.3 Embryofetal Toxicity

Based on its mechanism of action, HYMPAVZI may cause fetal harm when administered to a pregnant woman [see Clinical Pharmacology (12.1)]. Advise pregnant women of the potential risk to the fetus. Advise females of reproductive potential to use effective contraception during treatment with HYMPAVZI and for 2 months after the last dose [see Use in Specific Populations (8.1, 8.3)].

6 ADVERSE REACTIONS

The following clinically significant adverse reactions are described elsewhere in the labeling:

- Thromboembolic Events [see Warnings and Precautions (5.1)]
- Hypersensitivity [see Warnings and Precautions (5.2)]

6.1 Clinical Trials Experience

Because clinical trials are conducted under widely varying conditions, adverse reaction rates observed in the clinical trials of a drug cannot be directly compared to rates in the clinical trials of another drug and may not reflect the rates observed in practice.

The safety of HYMPAVZI was evaluated in adolescent and adult patients with severe hemophilia A or B without inhibitors (coagulation factor activity <1%) enrolled in the BASIS study [see Clinical Studies (14.1)]. Patients (N = 116) received HYMPAVZI prophylaxis 300 mg loading dose followed by 150 mg every week starting at Day 8 administered subcutaneously. Among patients receiving HYMPAVZI, 97% were exposed for 6 months or longer and 75% were exposed for at least 1 year.

A serious adverse reaction of peripheral swelling occurred in one patient.

Table 1 summarizes the adverse reactions reported in ≥3% of patients who received HYMPAVZI prophylaxis.

Table 1. Adverse Reactions Reported in ≥3% of Patients Treated with HYMPAVZI [During BASIS trial 12-month active treatment phase]
Adverse Reaction | Number of Patients; n (%); (N = 116)
Injection site reaction | 11 (9)
Headache | 8 (7)
Pruritus | 4 (3)

A serious adverse reaction of venous thrombosis occurred in 0.9% of patients (1/116) treated with HYMPAVZI in the open-label extension study [see Clinical Studies (14.1)].

7 DRUG INTERACTIONS

Partial Thromboplastin Time (aPTT) and Prothrombin Time (PT)
No clinically significant differences in standard measures of coagulation including activated partial thromboplastin time (aPTT) and prothrombin time (PT) were observed following marstacimab‑hncq therapy.

8 USE IN SPECIFIC POPULATIONS

8.1 Pregnancy

Risk Summary
Based on its mechanism of action, HYMPAVZI may cause fetal harm when administered to a pregnant woman [see Clinical Pharmacology (12.1)]. There are no available data on HYMPAVZI use in pregnant women to evaluate for a drug-associated risk of major birth defects, miscarriage or other adverse maternal or fetal outcomes. Female animal reproduction studies have not been conducted with HYMPAVZI. Although there are no data on marstacimab‑hncq, monoclonal antibodies can be actively transported across the placenta, and marstacimab‑hncq may cause fetal harm.

The background risk of major birth defects and miscarriage for the indicated populations is unknown. All pregnancies have a background risk of birth defect, loss, or other adverse outcomes. In the U.S. general population, the estimated background risk of major birth defects and miscarriage in clinically recognized pregnancies is 2% to 4% and 15% to 20%, respectively.

8.2 Lactation

Risk Summary
There are no data on the presence of marstacimab‑hncq in either human or animal milk, the effects on the breastfed child, or the effects on milk production.

Endogenous maternal IgG and monoclonal antibodies are known to be present in human milk. The effects of local gastrointestinal exposure and limited systemic exposure in the breastfed child to marstacimab‑hncq are unknown.

The developmental and health benefits of breastfeeding should be considered along with the mother's clinical need for HYMPAVZI and any potential adverse effects on the breastfed infant from HYMPAVZI or from the underlying maternal condition.

8.3 Females and Males of Reproductive Potential

HYMPAVZI may cause fetal harm when administered to a pregnant woman [see Use in Specific Populations (8.1)].

Pregnancy Testing
Verify the pregnancy status of females of reproductive potential prior to initiating HYMPAVZI treatment.

Contraception
Females
Advise female patients of reproductive potential to use effective contraception during treatment with HYMPAVZI and for 2 months after the last dose.

8.4 Pediatric Use

The safety and effectiveness of HYMPAVZI to prevent or reduce the frequency of bleeding episodes in hemophilia A or B without inhibitors have been established in pediatric patients aged 12 years and older [see Clinical Studies (14.1)]. Use of HYMPAVZI for this indication is supported by evidence from an open‑label, multi‑center phase 3 study in 19 adolescents and 97 adults with hemophilia without inhibitors.

The safety and effectiveness of HYMPAVZI have not been established in pediatric patients younger than 12 years old.

8.5 Geriatric Use

One patient 65 years of age and older was enrolled in the clinical studies for hemophilia A or B without inhibitors [see Clinical Studies (14.1)]. Clinical studies of HYMPAVZI did not include sufficient numbers of subjects aged 65 years and over to determine whether they respond differently from younger subjects.

11 DESCRIPTION

Marstacimab‑hncq is a tissue factor pathway inhibitor (TFPI) antagonist, human monoclonal immunoglobulin G Type 1 (IgG1) antibody. Marstacimab‑hncq is produced by Chinese hamster ovary (CHO) cells by recombinant DNA technology and has a molecular mass of approximately 146 kDa.

HYMPAVZI (marstacimab‑hncq) injection is supplied as a sterile, preservative-free solution for subcutaneous administration. The drug product is supplied as either a single-dose 150 mg/mL prefilled syringe or as a single‑dose 150 mg/mL prefilled pen. The solution of marstacimab‑hncq is clear and colorless to light yellow with a pH of 5.8.

Each 150 mg/mL prefilled syringe or prefilled pen delivers 1 mL of HYMPAVZI. Each 1 mL of HYMPAVZI contains 150 mg of marstacimab‑hncq, and the inactive ingredients edetate disodium (0.05 mg), histidine (1.12 mg), L-histidine monohydrochloride (2.67 mg), polysorbate 80 (0.2 mg), and sucrose (85 mg), in Water for Injection, USP.

12 CLINICAL PHARMACOLOGY

12.1 Mechanism of Action

Marstacimab‑hncq is a human monoclonal IgG1 antibody directed against the Kunitz domain 2 (K2) of TFPI to neutralize TFPI activity and enhance coagulation. TFPI is the primary inhibitor of the extrinsic coagulation cascade and negatively regulates thrombin generation within the extrinsic pathway of coagulation by inactivating the protease functions of FXa/FVIIa/TF complex. TFPI binds to and inhibits the factor Xa active site via its second Kunitz inhibitor domain (K2).

12.2 Pharmacodynamics

Marstacimab‑hncq causes an increase in total TFPI (comprised of free TFPI and TFPI bound to marstacimab) and downstream biomarkers of thrombin generation such as prothrombin fragments 1+2, peak thrombin, and D‑Dimer in patients with hemophilia. These changes were observed and persisted over a 7-day period following a single subcutaneous dose and were reversible after treatment discontinuation.

12.3 Pharmacokinetics

Estimated mean marstacimab‑hncq Cmin,ss, Cmax,ss, and Cavg,ss for adults and adolescents weighing at least 35 kg following marstacimab‑hncq 150 mg subcutaneous once-weekly administration are shown in Table 2. Marstacimab‑hncq area under the plasma concentration-time curve (AUC) and maximum plasma concentration (Cmax) increase in a greater than dose-proportional manner over the dose range of 100 mg to 450 mg (0.67 to 3 times the approved recommended dosage).

Mean steady-state accumulation ratio for marstacimab‑hncq is approximately 4 to 5. Marstacimab‑hncq steady‑state concentrations are achieved by approximately 60 days (8th or 9th subcutaneous dose) when administered once weekly.

Table 2. Steady-State Marstacimab‑hncq Plasma Concentrations Following Once-Weekly Subcutaneous Administration of 150 mg (with a Loading Dose of 300 mg Subcutaneous)
Parameter | Adults | Adolescents
Cmin,ss (mcg/mL) | 13.7 (90.4%) | 27.3 (53.2%)
Cmax,ss (mcg/mL) | 17.9 (77.5%) | 34.7 (48.5%)
Cavg,ss (mcg/mL) | 16.5 (81.2%) | 32.1 (49.5%)
• Data are presented as arithmetic mean (%CV).
• Cmin,ss = minimum plasma concentration at steady state; Cmax,ss = maximum plasma concentration at steady state; Cavg,ss = average plasma concentration at steady state.

Absorption
Bioavailability of marstacimab‑hncq following subcutaneous administration is approximately 71%. Median Tmax ranges from 23 to 59 hours following multiple subcutaneous administrations of marstacimab‑hncq to patients with hemophilia. No clinically significant differences were seen in marstacimab‑hncq bioavailability when administered subcutaneously in the arm, thigh or abdomen.

Distribution
Marstacimab‑hncq steady-state apparent volume of distribution is 8.6 L in patients with hemophilia.

Elimination
Marstacimab-hncq is cleared via linear and non-linear mechanisms. Marstacimab‑hncq exhibited non‑linear pharmacokinetics due to target-mediated drug disposition (TMDD) which occurs when it forms marstacimab‑hncq/TFPI complex. Once the target becomes saturated, linear pathway (i.e., catabolism) dominates.

Based on population pharmacokinetic analysis, 90% of marstacimab is expected to be eliminated by the end of approximately 1 month after the last dose (median time for 50% of drug to be eliminated is approximately 7 to 10 days).

Metabolism
Marstacimab‑hncq is expected to be metabolized into small peptides and amino acids by catabolic pathways in the same manner as endogenous IgG.

Specific Populations
No clinically significant differences in pharmacokinetics of marstacimab‑hncq were observed based on race, hemophilia type (A and B), mild renal impairment (eGFR of 60 to 89 mL/min/1.73 m^2), and mild hepatic impairment (total bilirubin >1× to ≤1.5× ULN). The effects of geriatric age (>65 years), moderate to severe renal (eGFR <59 mL/min/1.73 m^2) and moderate to severe hepatic (Child Pugh class B and C) impairment on marstacimab‑hncq pharmacokinetics are unknown.

Body Weight
Body weight was a significant covariate impacting the pharmacokinetics of marstacimab‑hncq. Marstacimab‑hncq exposures over the body weight range of 35 to 120 kg show a trend for increase in exposure with decrease in body weight. However, dose adjustment based on body weight is not required.

Pediatric Patients
Marstacimab‑hncq clearance (CL) was 29% lower in adolescents (12 to <18 years of age) compared to adults (18 years and older). No clinically significant difference in adolescent marstacimab‑hncq CL (L/hr/kg) compared to adults was observed after adjusting for body weight.

12.6 Immunogenicity

The observed incidence of anti-drug antibodies is highly dependent on the sensitivity and the specificity of the assay. Differences in assay methods preclude meaningful comparisons of the incidence of anti-drug antibodies (ADA) in the studies described below with the incidence of ADA in other studies, including those of marstacimab‑hncq or of other marstacimab products.

During the 12-month active treatment phase in the BASIS study, 23 of the 116 (19.8%) ADA‑evaluable marstacimab‑hncq‑treated patients developed ADAs. Among the 23 patients who tested positive for ADA, 6 patients (26%) developed neutralizing antibodies (NAbs) against marstacimab‑hncq. Subjects who received marstacimab‑hncq and developed anti-marstacimab-hncq antibodies had reduced marstacimab-hncq steady‑state concentrations, geometric mean decrease in the range of 24% to 50%, compared to those who did not develop anti‑marstacimab‑hncq antibodies through the course of the treatment period.

There was no identified clinically significant effect of ADAs, including NAbs, on safety or efficacy of marstacimab‑hncq over the treatment duration of 12 months.

13 NONCLINICAL TOXICOLOGY

13.1 Carcinogenesis, Mutagenesis, Impairment of Fertility

No studies have been conducted to assess marstacimab‑hncq for the potential for carcinogenicity or mutagenicity. Marstacimab‑hncq did not affect fertility when administered as a repeat dose to male rats at doses up to 1000 mg/kg/dose and an exposure margin of 212-times the exposure at a clinical dose of 300 mg subcutaneous weekly. No effects were observed in male or female reproductive organs in the repeat‑dose toxicity studies of up to 6 months in duration in rats and 3 months in duration in cynomolgus monkeys at doses of 1000 mg/kg/dose and 500 mg/kg/dose and exposure margins at least 201- and 219-times, respectively, the AUC exposure at a clinical dose of 300 mg subcutaneous weekly.

14 CLINICAL STUDIES

14.1 Hemophilia A without FVIII Inhibitors or Hemophilia B without FIX Inhibitors

The efficacy of HYMPAVZI was established in 116 adult and pediatric patients (aged 12 years and older and ≥35 kg) with severe hemophilia A without FVIII inhibitors or severe hemophilia B without FIX inhibitors enrolled in the BASIS study (NCT03938792), an open-label, multi-center, two-phase study. Severe hemophilia is defined as factor activity less than 1%. Patients with a history of coronary artery disease, venous or arterial thrombosis or ischemic disease were excluded from the study.

Following screening, patients entered a 6-month observation phase and were enrolled to two cohorts based on the factor replacement treatment they were receiving prior to study entry: on‑demand or routine prophylaxis. Patients who completed the observation phase were to receive 12 months of HYMPAVZI. Of the 116 patients who received HYMPAVZI, 33 patients were in the on‑demand treatment cohort and 83 were in the prophylactic treatment with FVIII or FIX cohort during the observation phase. Patients who completed the 12‑month BASIS study were eligible to enroll in an open-label extension study (NCT05145127).

Patients received an initial 300 mg loading dose of HYMPAVZI followed by maintenance doses of 150 mg of HYMPAVZI once weekly for 12 months. Dose escalation to 300 mg of HYMPAVZI once weekly was permitted after 6 months of treatment in patients weighing ≥50 kg and experiencing ≥2 breakthrough bleeds. Fourteen (12%) underwent dose escalation.

The mean annualized bleeding rates (ABRs) for treated bleeds were 39.86 and 7.90 in the observational phase for the on-demand and prophylaxis cohorts, respectively. All patients in the on-demand cohort had one or more target joints at study entry and 36% had 3 or more target joints at study entry. In the routine prophylaxis cohort, 57% of the patients had one or more target joints at study entry and 16% had 3 or more target joints at study entry.

The efficacy of HYMPAVZI for each cohort was based upon the ABR of treated bleeds during treatment with HYMPAVZI compared to ABR during the observational phase. Other objectives of the study included evaluation of HYMPAVZI prophylaxis on the incidences of spontaneous bleeds, joint bleeds, target joint bleeds and total bleeds.

Among the 116 patients treated with HYMPAVZI in the BASIS study, the mean age was 32 years (range 13 to 66); 19 patients were 12 to <18 years of age and all were male. Fifty-six (56) patients were White, 58 patients were Asian, 1 patient was Black or African American and 1 patient had race information unreported; 12 patients identified as Hispanic or Latino and 104 patients identified as not Hispanic or Latino. The patient population included 91 with hemophilia A and 25 with hemophilia B.

Patients with On-Demand Factor-Based Therapy in Observational Phase
Table 3 shows the efficacy results of HYMPAVZI prophylaxis compared with on-demand factor-based therapy. HYMPAVZI prophylaxis demonstrated superiority over on-demand factor-based therapy in incidences of treated bleeds, spontaneous bleeds, joint bleeds, total bleeds and target joint bleeds.

Table 3. Comparison of Annualized Bleeding Rate with HYMPAVZI Prophylaxis Versus On‑Demand Factor-Based Therapy in Patients ≥12 Years of Age without Factor VIII or Factor IX Inhibitors
Endpoints in the Order of Testing Hierarchy | On-Demand Factor-Based; Therapy During 6-Month OP; (N = 33) | HYMPAVZI Prophylaxis; During 12-Month ATP; (N = 33)
Treated Bleeds (Primary)
ABR, model-based (95% CI) | 39.86 (33.05, 48.07) | 3.20 (2.10, 4.88)
Ratio vs. OD (95% CI); p-value | 0.080 (0.057, 0.113) <0.0001
Spontaneous Bleeds, Treated
ABR, model-based (95% CI) | 32.63 (25.79, 41.28) | 2.45 (1.62, 3.72)
Ratio vs. OD (95% CI); p-value | 0.075 (0.053, 0.107); <0.0001
Joint Bleeds, Treated
ABR, model-based (95% CI) | 34.52 (27.84, 42.79) | 2.85 (1.82, 4.46)
Ratio vs. OD (95% CI); p-value | 0.083 (0.057, 0.119); <0.0001
Total Bleeds, Treated & Untreated
ABR, model-based (95% CI) | 49.97 (42.09, 59.32) | 7.41 (5.10, 10.75)
Ratio vs. OD (95% CI); p-value | 0.148 (0.111, 0.198); <0.0001
Target Joint Bleeds, Treated
ABR, model-based (95% CI) | 24.38 (18.27, 32.53) | 1.84 (1.07, 3.18)
Ratio vs. OD (95% CI); p-value | 0.076 (0.048, 0.119); <0.0001
• p-value for the null hypothesis that the ratio = 0.5.
• The estimated mean, ratio, and confidence intervals (CIs) for the ABR come from a negative binomial regression model.
• Bleed definitions adapted based on ISTH criteria: Treated bleeds = bleeds treated with FVIII or FIX; Total bleeds = bleeds treated and not treated with FVIII or FIX
• ABR = Annualized Bleeding Rate; CI = Confidence Interval; OD = On-Demand; OP = Observational Phase; ATP = Active Treatment Phase

Patients with Routine Prophylactic Factor-Based Therapy
Table 4 shows the efficacy results of HYMPAVZI prophylaxis compared with routine prophylactic factor‑based therapy. HYMPAVZI prophylaxis demonstrated non-inferiority to routine prophylactic factor‑based therapy as measured by ABR of treated bleeds as well as incidences of spontaneous bleeds, joint bleeds, target joint bleeds and total bleeds.

Table 4. Comparison of Annualized Bleeding Rate with HYMPAVZI Prophylaxis Versus Previous Routine Factor-Based Prophylaxis in Patients ≥12 Years of Age without Factor VIII or Factor IX Inhibitors
Endpoints in the Order of Testing; Hierarchy | Routine Factor-Based; Prophylaxis During; 6-Month OP; (N = 83) | HYMPAVZI Prophylaxis During 12-Month ATP; (N = 83)
Treated Bleeds (Primary)
ABR, model-based (95% CI) | 7.90 (5.14, 10.66) | 5.09 (3.40, 6.78)
Difference vs. RP (95% CI) | -2.81 (-5.42, -0.20)
Spontaneous Bleeds, Treated
ABR, model-based (95% CI) | 5.89 (3.57, 8.22) | 3.78 (2.25, 5.31)
Difference vs. RP (95% CI) | -2.11 (-4.26, 0.03)
Joint Bleeds, Treated
ABR, model-based (95% CI) | 5.69 (3.36, 8.02) | 4.13 (2.59, 5.67)
Difference vs. RP (95% CI) | -1.55 (-3.73, 0.62)
Total Bleeds, Treated & Untreated
ABR, model-based (95% CI) | 8.90 (6.02, 11.77) | 5.98 (4.14, 7.82)
Difference vs. RP (95% CI) | -2.91 (-5.66, -0.17)
Target Joint Bleeds, Treated
ABR, model-based (95% CI) | 3.37 (1.60, 5.15) | 2.51 (1.26, 3.76)
Difference vs. RP (95% CI) | -0.87 (-2.42, 0.69)
• The protocol specified non-inferiority criterion (upper bound of the 95% CI for the difference) was 2.5 for treated bleeds, spontaneous bleeds, joint bleeds; 1.2 for target joint bleeds; 2.9 for total bleeds.
• The estimated mean, difference, and confidence intervals (CIs) for the ABR come from negative binomial regression model.
• Bleed definitions adapted based on ISTH criteria: Treated bleeds = bleeds treated with FVIII or FIX; Total bleeds = bleeds treated and not treated with FVIII or FIX
• ABR = Annualized Bleeding Rate; CI = Confidence Interval; OP = Observational Phase; ATP = Active Treatment Phase; RP = Routine Prophylaxis

16 HOW SUPPLIED/STORAGE AND HANDLING

16.1 How Supplied

HYMPAVZI (marstacimab‑hncq) injection is a sterile, preservative-free, clear and colorless to light yellow solution available as a 150 mg/mL single-dose prefilled syringe or pen for subcutaneous administration.

Prefilled Syringe
Each carton (NDC 0069-1510-01) contains one single-dose prefilled syringe (Type I glass) with a plunger stopper (chlorobutyl elastomer) and a stainless steel 27 gauge, ½ inch staked needle with a rigid needle shield (thermoplastic elastomer).

Prefilled Pen
Each carton (NDC 0069-2151-01) contains one single-dose prefilled pen with needle guard. The syringe inside the pen is made from Type I glass with a plunger stopper (chlorobutyl elastomer) and a stainless steel 27 gauge, ½ inch staked needle with a rigid needle shield (thermoplastic elastomer).

HYMPAVZI is not made with natural rubber latex.

16.2 Recommended Storage and Handling

- Store refrigerated at 36°F to 46°F (2°C to 8°C) in the original carton to protect from light.
- If needed, HYMPAVZI may be stored one time at room temperature [up to 86°F (30°C)] in its original carton to protect from light for up to 7 days. Once stored at room temperature, do not return to the refrigerator and discard after 7 days.
- Do not freeze.
- Do not shake.

17 PATIENT COUNSELING INFORMATION

- Advise the patient and/or caregivers to read the FDA-approved patient labeling (Patient Information and Instructions for Use).
- Ensure that patients and caregivers who will administer HYMPAVZI receive appropriate training and instruction on the proper storage, use and handling of HYMPAVZI from a healthcare professional.

Thromboembolic Events
Inform patients and/or caregivers that HYMPAVZI increases coagulation potential. Discuss the appropriate dosing of concomitant agents such as FVIII or FIX with the patient prior to starting on HYMPAVZI prophylaxis [see Warnings and Precautions (5.1)]. Advise the patient to discontinue HYMPAVZI and seek immediate medical attention if any signs or symptoms of thromboembolism occur.

Hypersensitivity
Inform patients and/or caregivers that hypersensitivity reactions such as rash and pruritus are possible. Advise patients to discontinue HYMPAVZI and seek immediate emergency treatment if a severe hypersensitivity reaction occurs [see Warnings and Precautions (5.2)].

Pregnancy
Advise female patients of reproductive potential to use effective contraception during treatment with HYMPAVZI and for 2 months after the last dose. Advise patients to report known pregnancies [see Warnings and Precautions (5.3), Use in Specific Populations (8.1, 8.3)].

This product’s labeling may have been updated. For the most recent prescribing information, please visit www.pfizer.com.

For medical information about HYMPAVZI, please visit www.pfizermedinfo.com or call 1-800-438-1985.

US License No. 2001
Distributed by
Pfizer Labs
Division of Pfizer Inc.
New York, NY 10001
LAB-1556-3.0

PATIENT INFORMATION

HYMPAVZI (him-PAV-zee)

(marstacimab-hncq)

injection, for subcutaneous use

Important information: Before you start using HYMPAVZI, it is very important to talk to your healthcare provider about using factor VIII and factor IX products (products that help blood clot but work in a different way than HYMPAVZI). You may need to use factor VIII or factor IX medicines to treat episodes of breakthrough bleeding during treatment with HYMPAVZI. Carefully follow your healthcare provider’s instructions regarding when to use factor VIII or factor IX medicines and the prescribed dose during your treatment with HYMPAVZI.

What is HYMPAVZI?

HYMPAVZI is a prescription medicine used regularly to prevent or reduce the frequency of bleeding episodes in adults and children 12 years of age and older with hemophilia A without factor VIII inhibitors or hemophilia B without factor IX inhibitors.

It is not known if HYMPAVZI is safe and effective in children younger than 12 years old.

Before using HYMPAVZI, tell your healthcare provider about all of your medical conditions, including if you:

- have a planned surgery. Your healthcare provider may stop treatment with HYMPAVZI before your surgery. Talk to your healthcare provider about when to stop using HYMPAVZI and when to start it again if you have a planned surgery.
- have a severe short-term (acute) illness such as an infection or injury.
- have been told that you have a risk for blood clots.
- are pregnant or plan to become pregnant. HYMPAVZI may harm your unborn baby.
Females who are able to become pregnant:
  1. Your healthcare provider will do a pregnancy test before you start your treatment with HYMPAVZI.
  2. You should use effective birth control (contraception) during treatment with HYMPAVZI and for 2 months after the last dose of HYMPAVZI.
  3. Tell your healthcare provider right away if you become pregnant or think that you may be pregnant during treatment with HYMPAVZI.
- are breastfeeding or plan to breastfeed. It is not known if HYMPAVZI passes into your breast milk.

Tell your healthcare provider about all the medicines you take, including prescription medicines, over‑the‑counter medicines, vitamins, and herbal supplements.

Know the medicines you take. Keep a list of them to show your healthcare provider and pharmacist when you get a new medicine.

How should I use HYMPAVZI?

See the detailed “Instructions for Use” that comes with your HYMPAVZI for information on how to inject a dose of HYMPAVZI, and how to properly throw away (dispose of) used HYMPAVZI prefilled syringe or HYMPAVZI prefilled pen.

- Use HYMPAVZI exactly as prescribed by your healthcare provider.
- Your healthcare provider will provide instructions for stopping (discontinuing) your current treatment when switching from factor- or non-factor-based medicines to HYMPAVZI.
- HYMPAVZI is given as an injection under your skin (subcutaneous injection) by you or your caregiver.
- Your healthcare provider should show you or your caregiver how to inject HYMPAVZI before you inject yourself for the first time.
- Do not attempt to inject yourself or another person unless you have been taught how to do so by a healthcare provider.
- Your first dose (loading dose) of HYMPAVZI is 300 mg (two 150 mg injections). Then you will inject a weekly (maintenance) dose as prescribed by your healthcare provider.
- Inject HYMPAVZI 1 time a week on the same day each week. Inject HYMPAVZI at any time of day.
- Your healthcare provider will provide information on the treatment of breakthrough bleeding during your treatment with HYMPAVZI. Do not use HYMPAVZI to treat breakthrough bleeding.
- If you miss a maintenance dose of 150 mg of HYMPAVZI:
  - Give the dose as soon as possible before the next scheduled dose, and then continue with your usual 150 mg weekly dosing schedule. You may inject your next dose at your regularly scheduled time or continue dosing based on the new day you injected your missed dose. In case you are not sure when to inject HYMPAVZI, call your healthcare provider.
  - If more than 13 days have passed since your last dose was given, call your healthcare provider right away for dosing instructions.
- If you miss 1 or more doses of maintenance dose of 300 mg of HYMPAVZI:
  - Give a dose as soon as possible, and then continue with your 300 mg weekly dosing schedule. You may inject your next dose at your regularly scheduled time or continue dosing based on the new day you injected your missed dose. In case you are not sure when to inject HYMPAVZI, call your healthcare provider.

What are the possible side effects of HYMPAVZI?

HYMPAVZI may cause serious side effects, including:

- blood clots (thromboembolic events). HYMPAVZI may increase the risk for your blood to clot in blood vessels in your arm, leg, lung, or head and can be life-threatening. Blood clots have happened in people using HYMPAVZI. You may have an increased risk of blood clots if you have certain risk factors. Stop using HYMPAVZI and get medical help right away if you develop any of these signs or symptoms of blood clots:

- swelling or pain in arms or legs
- redness or discoloration in your arms or legs
- shortness of breath
- pain in chest or upper back
- fast heart rate
- cough up blood

- feel faint
- headache
- numbness in your face
- eye pain or swelling
- trouble seeing

- allergic reactions. HYMPAVZI may cause allergic reactions, including rash and itching. Stop using HYMPAVZI and get medical help right away if you develop any of the following symptoms of a severe allergic reaction:

- swelling of your face, lips, mouth, or tongue
- trouble breathing
- wheezing

- dizziness or fainting
- fast heartbeat or pounding in your chest
- sweating

The most common side effects of HYMPAVZI include:

- swelling, hardening, redness, bruising, and pain at injection site
- headache
- itching

These are not all of the possible side effects of HYMPAVZI.

Call your doctor for medical advice about side effects. You may report side effects to FDA at 1-800-FDA-1088.

How should I store HYMPAVZI?

- Store HYMPAVZI in a refrigerator at 36°F to 46°F (2°C to 8°C).
- Store HYMPAVZI in the original carton to protect from light.
- If needed, HYMPAVZI may be stored one time at room temperature up to 86°F (30°C) in its original carton for up to 7 days. Do not return HYMPAVZI to the refrigerator after storing at room temperature.
- Throw away (dispose of) HYMPAVZI that has been left out of the refrigerator for more than 7 days.
- Do not freeze HYMPAVZI.
- Do not shake HYMPAVZI.

Keep HYMPAVZI and all medicines out of the reach of children.

General information about the safe and effective use of HYMPAVZI.

Medicines are sometimes prescribed for purposes other than those listed in a Patient Information leaflet. Do not use HYMPAVZI for a condition for which it was not prescribed. Do not give HYMPAVZI to other people, even if they have the same symptoms that you have. It may harm them. You can ask your pharmacist or healthcare provider for information about HYMPAVZI that is written for health professionals.

What are the ingredients in HYMPAVZI?

Active ingredient: marstacimab‑hncq

Inactive ingredients: edetate disodium, histidine, L-histidine monohydrochloride, polysorbate 80, sucrose, and water for injection

This product's labeling may have been updated. For the most recent prescribing information, please visit www.pfizer.com.

US License No. 2001
Distributed by: Pfizer Labs, Division of Pfizer Inc., New York, NY 10001
LAB-1575-2.0
For more information, go to website www.HYMPAVZI.com or call 1-800-438-1985.

This Patient Information has been approved by the U.S. Food and Drug Administration. Revised: 09/2025

INSTRUCTIONS FOR USE
HYMPAVZI™ (him-PAV-zee)
(marstacimab-hncq)
injection, for subcutaneous use
single-dose prefilled syringe

This Instructions for Use contains information on how to inject HYMPAVZI.

Read this Instructions for Use carefully before using HYMPAVZI Prefilled Syringe and each time you get a refill prescription as there may be new information.

Your healthcare provider should show you or your caregiver how to prepare and inject a dose of HYMPAVZI the right way before you use it for the first time. Do not inject yourself or someone else until you have been shown how to inject HYMPAVZI.

Important Information You Need to Know Before Injecting HYMPAVZI

- Each HYMPAVZI Prefilled Syringe is a Single-Dose Prefilled Syringe (called “Syringe” in this Instructions for Use). The HYMPAVZI Prefilled Syringe contains 150 mg of HYMPAVZI for injection under the skin (subcutaneously).
- Do not inject HYMPAVZI into a vein.
- To help you remember when to inject HYMPAVZI, you can mark your calendar ahead of time. Call your healthcare provider if you or your caregiver have any questions about the right way to inject HYMPAVZI, or call the helpline at 1‑888‑496‑7289 (1‑888 HYMPAV‑Z).
- Use HYMPAVZI exactly as prescribed by your healthcare provider.
- HYMPAVZI is not made with natural rubber latex.

Storing HYMPAVZI

- Store HYMPAVZI in a refrigerator at 36°F to 46°F (2°C to 8°C).
- Store HYMPAVZI in the original carton to protect from light.
- If needed, HYMPAVZI may be stored one time at room temperature, up to 86°F (30°C) in the original carton for up to 7 days. Do not return HYMPAVZI to the refrigerator after storing at room temperature.
- Throw away (dispose of) HYMPAVZI that has been left out of the refrigerator for more than 7 days.
- Do not freeze HYMPAVZI.
- Do not shake HYMPAVZI.
- Do not use past the expiration date (Exp) printed on the HYMPAVZI Prefilled Syringe.
- Keep HYMPAVZI and all medicines out of the reach of children.

Supplies Needed For HYMPAVZI Injection

Gather the following supplies on a clean flat surface:

Included in the carton:

- 1 HYMPAVZI Prefilled Syringe

Not included in the carton:

- 1 alcohol swab
- 1 cotton ball or gauze pad
- 1 FDA-cleared sharps disposal container for Syringe disposal (see “Step 11 – Disposal of Syringe” and “Safe Syringe Disposal” information section)

HYMPAVZI Prefilled Syringe

Always hold HYMPAVZI Prefilled Syringe by the barrel to prevent damage.

Preparing to Inject HYMPAVZI

Step 1 – Getting Ready

- Remove the Syringe from its carton and keep out of direct sunlight.
- Make sure the name HYMPAVZI appears on the carton and Syringe label.
- Check the Syringe for any visible damage such as cracks or leaks.
- Wash and dry your hands.
- Do not remove the needle cover until you are ready to inject.
- Throw away (dispose of) the Syringe if it is damaged, or if the Syringe or the carton containing the Syringe has been dropped.
- Do not use the Syringe if:
  - it has been stored in direct light. Exposure to room light during dose preparation and injection is acceptable.
  - it has been frozen or thawed or it has been out of the refrigerator for more than 7 days.

Note: For a more comfortable injection, allow the Syringe to warm up to room temperature [up to 86°F (30°C)] in the carton away from direct sunlight for about 15 to 30 minutes.

Do not use any other methods to warm up the Syringe, such as warming the Syringe in a microwave or hot water.

Step 2 – Check Expiration Date

- Check the expiration date (Exp) printed on the Syringe label.
- Do not use if the expiration date (Exp) has passed.

Step 3 – Check Medicine

- Gently tilt the Syringe back and forth.
- Look carefully at the medicine in the Syringe.
  - The medicine should be clear and colorless to light yellow.
  - Do not use the Syringe if the medicine is cloudy, dark yellow, or contains flakes or particles.

Note: It is normal to see air bubbles in the Syringe.

If you have any questions about the medicine, contact your healthcare provider.

Step 4 – Choose and Clean Your Injection Site

- Choose an injection site on your stomach area (abdomen) or front of thigh unless a different site has been suggested by your healthcare provider. HYMPAVZI may also be injected into the back of your upper arms by a healthcare provider or caregiver only. Keep at least 2 inches away from your belly button.
- Change (rotate) the injection site each time you give yourself an injection of HYMPAVZI and away from any other medicine given under your skin. You may use the same area of your body but be sure to choose a different injection site in that area.
- Clean the injection site with soap and water, or an alcohol swab.
- Allow the site to air dry. Do not touch, fan, or blow on the cleaned injection site.
- Do not inject HYMPAVZI into bony areas or areas on your skin that are bruised, red, sore (tender) or hard. Avoid injecting into areas with scars or stretch marks.
- Do not inject HYMPAVZI into a vein.
- Do not inject HYMPAVZI through your clothes.

Step 5 – Remove Cover

- Hold the Syringe by the barrel.
- Pull the needle cover straight off carefully.
- Put the needle cover into an FDA-cleared sharps disposal container right away. You will not need it again.
- Do not touch the needle or let it touch any surfaces.

Note: It is normal to see a few drops of medicine at the needle tip.

Caution: Handle the Syringe with care to avoid an accidental needle injury.

Injecting HYMPAVZI

Step 6 – Insert Needle

- Pinch your cleaned skin between your thumb and fingers to create a firm surface.
- Fully insert the needle into your skin at a 45° angle, as shown. Do not hold or push on the plunger while inserting the needle.

Keep your skin pinched throughout the injection.

Caution: If you change your mind where to inject after inserting the needle into your skin, you will need to throw away (dispose of) the Syringe and get a new HYMPAVZI Prefilled Syringe.

Step 7 – Inject Medicine

- Slowly inject all of HYMPAVZI by gently pushing the plunger rod all the way down, until the barrel is empty.

Step 8 – Remove Needle

- Pull the needle and Syringe out of your skin at the same angle as inserted.

Note: If you see a small drop of medicine on your skin, wait a little longer before removing the needle when you give your next injection.

Step 9 – Check Syringe

- Check the Syringe to make sure the gray plunger stopper is in the position shown.

If the gray plunger stopper is not in the position shown, this means you have not received a full dose. Call your healthcare provider for help.

Never re-insert the needle.

Do not inject another dose.

Step 10 – After Care

- Press lightly on the injection site for a few seconds with a clean cotton ball or gauze pad if you see a drop of blood.
- Do not rub the area.

Note: If bleeding does not stop, contact your healthcare provider.

Note: If your prescribed dose requires 2 injections of HYMPAVZI, repeat steps 1-10. Change (rotate) the injection site each time you give yourself an injection of HYMPAVZI. You may use the same area of your body but be sure to choose a different injection site in that area.

Step 11 – Disposal of Syringe

- Put the used Syringe in an FDA-cleared sharps disposal container right away after use.

Never re-cap the needle.

- Do not throw away (dispose of) Syringes in the household trash.

Note: If you do not have an FDA-cleared sharps disposal container, please see the “Safe Syringe Disposal” information section.

Safe Syringe Disposal

- Always throw away (dispose of) Syringes in a sharps disposal container. Do not dispose of Syringes in the household trash.
- If you do not have an FDA-cleared sharps disposal container, you may use a household container that:
  - is made of heavy-duty plastic,
  - can be closed with a tight-fitting, puncture-resistant lid, without sharps being able to come out,
  - is upright and stable during use,
  - is leak-resistant, and
  - is properly labeled to warn of hazardous waste inside the container.
- When your sharps disposal container is almost full, you will need to follow your community guidelines for the right way to throw away (dispose of) your sharps disposal container. There may be state or local laws about how you should throw away used needles and syringes. For more information about safe sharps disposal, and for specific information about safe sharps disposal for the state you live in, go to the FDA’s website at: http://www.fda.gov/safesharpsdisposal.
- Do not recycle your used sharps disposal container.

US License No. 2001
Distributed by
Pfizer Labs
Division of Pfizer Inc.
New York, NY 10001
LAB-1576-2.0

For more information, go to www.pfizer.com or call 1-800-438-1985.

This Instructions for Use has been approved by the U.S. Food and Drug Administration. Revised: 09/2025

INSTRUCTIONS FOR USE
HYMPAVZI™ (him-PAV-zee)
(marstacimab-hncq)
injection, for subcutaneous use
single-dose prefilled pen

This Instructions for Use contains information on how to inject HYMPAVZI.

Read this Instructions for Use carefully before using HYMPAVZI Prefilled Pen and each time you get a refill prescription as there may be new information.

Your healthcare provider should show you or your caregiver how to prepare and inject a dose of HYMPAVZI the right way before you use it for the first time. Do not inject yourself or someone else until you have been shown how to inject HYMPAVZI.

Important Information You Need to Know Before Injecting HYMPAVZI

- Each HYMPAVZI Prefilled Pen is a Single-Dose Prefilled Pen (called “Pen” in this Instructions for Use). The HYMPAVZI Prefilled Pen contains 150 mg of HYMPAVZI for injection under the skin (subcutaneously).
- Do not inject HYMPAVZI into a vein.
- To help you remember when to inject HYMPAVZI, you can mark your calendar ahead of time. Call your healthcare provider if you or your caregiver have any questions about the right way to inject HYMPAVZI, or call the helpline at 1‑888‑496‑7289 (1‑888 HYMPAV‑Z).
- Use HYMPAVZI exactly as prescribed by your healthcare provider.
- HYMPAVZI is not made with natural rubber latex.

Storing HYMPAVZI

- Store HYMPAVZI in a refrigerator at 36°F to 46°F (2°C to 8°C).
- Store HYMPAVZI in the original carton to protect from light.
- If needed, HYMPAVZI may be stored one time at room temperature, up to 86°F (30°C) in the original carton for up to 7 days. Do not return HYMPAVZI to the refrigerator after storing at room temperature.
- Throw away (dispose of) HYMPAVZI that has been left out of the refrigerator for more than 7 days.
- Do not freeze HYMPAVZI.
- Do not shake HYMPAVZI.
- Do not use past the expiration date (EXP) printed on the HYMPAVZI Prefilled Pen.
- Keep HYMPAVZI and all medicines out of the reach of children.

Supplies Needed For HYMPAVZI Injection

Gather the following supplies on a clean flat surface:

Included in the carton:

- 1 HYMPAVZI Prefilled Pen

Not included in the carton:

- 1 alcohol swab
- 1 cotton ball or gauze pad
- 1 FDA-cleared sharps disposal container for Pen disposal (see “Step 10 – Disposal of Pen” and “Safe Pen Disposal” information section)

HYMPAVZI Prefilled Pen

Preparing to Inject HYMPAVZI

Step 1 – Getting Ready

- Remove the Pen from its carton and keep out of direct sunlight.
- Make sure the name HYMPAVZI appears on the carton and Pen label.
- Check the Pen for any visible damage such as cracks or leaks.
- Wash and dry your hands.
- Do not remove the cap until you are ready to inject.
- Throw away (dispose of) the Pen if it is damaged, or if the Pen or the carton containing the Pen has been dropped.
- Do not use the Pen if:
  - it has been stored in direct light. Exposure to room light during dose preparation and injection is acceptable.
  - it has been frozen or thawed or it has been out of the refrigerator for more than 7 days.

Note: For a more comfortable injection, allow the Pen to warm up to room temperature [up to 86°F (30°C)] in the carton away from direct sunlight for about 15 to 30 minutes.

Do not use any other methods to warm up the Pen, such as warming the Pen in a microwave or hot water.

Step 2 – Check Expiration Date

- Check the expiration date (EXP) printed on the Pen label.
- Do not use if the expiration date (EXP) has passed.

Step 3 – Check Medicine

- Look carefully at the medicine through the window on the Pen.
  - The medicine should be clear and colorless to light yellow.
  - Do not use the Pen if the medicine is cloudy, dark yellow, or contains flakes or particles.

Note: It is normal to see air bubbles in the window.

If you have any questions about the medicine, contact your healthcare provider.

Step 4 – Choose and Clean Your Injection Site

- Choose an injection site on your stomach area (abdomen) or front of thigh unless a different site has been suggested by your healthcare provider. HYMPAVZI may also be injected into your buttocks by a healthcare provider or caregiver only. Keep at least 2 inches away from your belly button.
- Change (rotate) the injection site each time you give yourself an injection of HYMPAVZI and away from any other medicine given under your skin. You may use the same area of your body but be sure to choose a different injection site in that area.
- Clean the injection site with soap and water, or an alcohol swab.
- Allow the site to air dry. Do not touch, fan, or blow on the cleaned injection site.
- Do not inject HYMPAVZI into bony areas or areas on your skin that are bruised, red, sore (tender) or hard. Avoid injecting into areas with scars or stretch marks.
- Do not inject HYMPAVZI into a vein.
- Do not inject HYMPAVZI through your clothes.

Step 5 – Twist Off Cap

- Twist and pull off the cap.
- Put the cap into an FDA-cleared sharps disposal container right away. You will not need it again.

Note:

  - It is normal to see a few drops of medicine at the needle tip.
  - The needle cover will stay inside the cap after cap removal.

Caution: Handle the Pen with care as it contains a needle.

Do not put or press your hand over the needle guard. Doing so may cause a needle injury.

Injecting HYMPAVZI

Step 6 – Inject Medicine

- Hold the Pen straight (at 90° angle) against your cleaned skin so you can see the window.
- Push the Pen down firmly straight against your skin and keep pushing until the injection is complete. You will hear the 1st click when the injection starts.
- Keep pushing the Pen firmly against your skin while the yellow bar moves across the window. You will hear a 2nd click when the injection is almost complete.
- Count slowly to 5 after you hear the 2nd click to make sure you get a full dose.

Do not remove the Pen from your skin until you have counted slowly to 5 after you hear the 2nd click and until the yellow marker completely fills the window (see “Step 7 – Remove Pen”).

Note: The needle goes into your skin as you push the Pen down. Your healthcare provider may suggest gently pinching your skin while you inject.

Note: If you do not hear a click when pushing the Pen against your skin, try pushing down harder. If you still cannot start the injection, get a new HYMPAVZI Prefilled Pen.

Caution: If you change your mind where to inject after inserting the needle into your skin, you will need to throw away (dispose of) the Pen and get a new HYMPAVZI Prefilled Pen.

Step 7 – Remove Pen

- Remove the Pen from your skin.
  - If you see a small drop of medicine on your skin, wait a little longer before removing the Pen when you give your next injection.

Note: After you remove the Pen from your skin, the needle guard will automatically cover the needle and lock in place.

The Pen cannot be reused.

Step 8 – Check Window

- Check the window to make sure all the medicine has been injected.

If the yellow bar is not in the position shown, this means you have not received a full dose. Call your healthcare provider for help.

Do not inject another dose.

Step 9 – After Care

- Press lightly on the injection site for a few seconds with a clean cotton ball or gauze pad if you see a drop of blood.
- Do not rub the area.

Note: If bleeding does not stop, contact your healthcare provider.

Note: If your prescribed dose requires 2 injections of HYMPAVZI, repeat steps 1-9. Change (rotate) the injection site each time you give yourself an injection of HYMPAVZI. You may use the same area of your body but be sure to choose a different injection site in that area.

Step 10 – Disposal of Pen

- Put the used Pen in an FDA-cleared sharps disposal container right away after use.
- Do not throw away (dispose of) Pens in the household trash.

Note: If you do not have an FDA-cleared sharps disposal container, please see the “Safe Pen Disposal” information section.

Safe Pen Disposal

- Always throw away (dispose of) Pens in a sharps disposal container. Do not dispose of Pens in the household trash.
- If you do not have an FDA-cleared sharps disposal container, you may use a household container that:
  - is made of heavy-duty plastic,
  - can be closed with a tight-fitting, puncture-resistant lid, without sharps being able to come out,
  - is upright and stable during use,
  - is leak-resistant, and
  - is properly labeled to warn of hazardous waste inside the container.
- When your sharps disposal container is almost full, you will need to follow your community guidelines for the right way to throw away (dispose of) your sharps disposal container. There may be state or local laws about how you should throw away used needles and Pens. For more information about safe sharps disposal, and for specific information about safe sharps disposal for the state you live in, go to the FDA’s website at: http://www.fda.gov/safesharpsdisposal.
- Do not recycle your used sharps disposal container.

US License No. 2001
Distributed by
Pfizer Labs
Division of Pfizer Inc.
New York, NY 10001

LAB-1577-2.0

For more information, go to www.pfizer.com or call 1-800-438-1985.

This Instructions for Use has been approved by the U.S. Food and Drug Administration. Revised: 09/2025

PRINCIPAL DISPLAY PANEL – 150 mg/mL Prefilled Pen

NDC 0069-2151-01

Pfizer

HYMPAVZITM
(marstacimab-hncq)
Injection

150 mg/mL

For Subcutaneous Use Only

Rx only

PRINCIPAL DISPLAY PANEL – 150 mg/mL Prefilled Pen Carton

NDC 0069-2151-01

1 single-dose prefilled pen

Pfizer

HYMPAVZI TM
(marstacimab-hncq)
Injection

150 mg/mL

For Subcutaneous Use Only
READ ENCLOSED INSTRUCTIONS BEFORE USE

This carton contains:
1 Prefilled Pen
1 Instructions for Use
1 Prescribing Information

Keep out of reach of children.

Rx only

PRINCIPAL DISPLAY PANEL - 150 mg/mL Prefilled Syringe

NDC 0069-1510-01

Single-Dose

HYMPAVZITM
(marstacimab-hncq)
Injection

150 mg/mL

For Subcutaneous Use Only

Rx only

Mfg. by Pfizer Inc.

US Lic. No. 2001

PRINCIPAL DISPLAY PANEL - 150 mg/mL Prefilled Syringe Carton

NDC 0069-1510-01

1 single-dose prefilled syringe

Pfizer

HYMPAVZI TM
(marstacimab-hncq)
Injection

150 mg/mL

For Subcutaneous Use Only
READ ENCLOSED INSTRUCTIONS BEFORE USE

This carton contains:
1 Prefilled Syringe
1 Instructions for Use
1 Prescribing Information

Keep out of reach of children.

Rx only